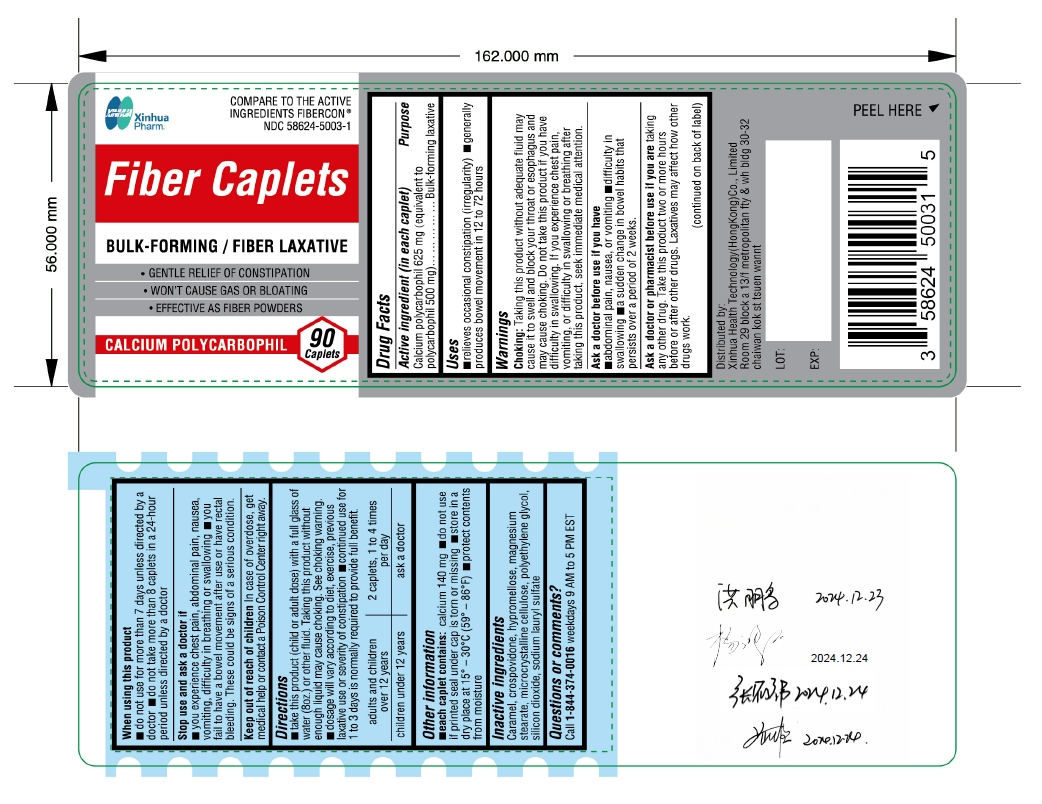 DRUG LABEL: Calcium Polycarbophil
NDC: 58624-5003 | Form: TABLET, FILM COATED
Manufacturer: SHANDONG XINHUA PHARMACEUTICAL CO., LTD.
Category: otc | Type: HUMAN OTC DRUG LABEL
Date: 20250102

ACTIVE INGREDIENTS: CALCIUM POLYCARBOPHIL 625 mg/1 1
INACTIVE INGREDIENTS: CARAMEL; SILICON DIOXIDE; SODIUM LAURYL SULFATE; CROSPOVIDONE; MICROCRYSTALLINE CELLULOSE; HYPROMELLOSES; MAGNESIUM STEARATE; POLYETHYLENE GLYCOL 400

Fiber Caplets
Calcium polycarbophil 625 mg

Drug Facts

Active ingredient (in each caplet)

Calcium polycarbophil 625 mg (equivalent to polycarbophil 500 mg)

Purpose

Bulk-forming laxative

Uses

relieves occasional constipation (irregularity)

generally produces bowel movement in 12 to 72 hours

WARNINGS

Choking: Taking this product without adequate fluid may cause it to swell and block your throat or esophagus and may cause choking. Do not take this product if you have difficulty in swallowing. If you experience chest pain, vomiting, or difficulty in swallowing or breathing after taking this product, seek immediate medical attention.

Ask a doctor before use if you have

abdominal pain, nausea, or vomiting

difficulty in swallowing

a sudden change in bowel habits that persists over a period of 2 weeks

Ask a doctor or pharmacist before use if you are

taking any other drug. Take this product two or more hours before or after other drugs. Laxatives may affect how other drugs work.

When using this product

do not use for more than 7 days unless directed by a doctor
do not take more than 8 caplets in a 24-hour period unless directed by a doctor

Stop use and ask a doctor if

you experience chest pain, abdominal pain, nausea, vomiting, difficulty in breathing or swallowing

you fail to have a bowel movement after use or have rectal bleeding. These could be signs of a serious condition.

Keep out of reach of children.

OVERDOSAGE

In case of overdose, get medical help or contact a Poison Control Center right away.

Directions

take this product (child or adult dose) with a full glass of water (8oz.) or other fluid. Taking this product without enough liquid my cause choking. See choking warning.
dosage will vary according to diet, exercise, previous laxative use or severity of constipation
continued use for 1 to 3 days is normally required to provide full benefit

adults and children over 12 years | 2 caplets, 1 to 4 times per day
children under 12 years | ask a doctor

Other information

 each caplet contains: calcium 140 mg

do not use if printed seal under cap is torn or missing store in a dry place at 15° – 30°C (59° – 86°F)
protect contents from moisture

INACTIVE INGREDIENT

Caramel, crospovidone, hypromellose, magnesium stearate, microcrystalline cellulose, polyethylene glycol, silicon dioxide, sodium lauryl sulfate

Questions or comments?

Call 1-844-374-0016 weekdays 9 AM to 5 PM EST

PACKAGE LABEL

Fiber Caplets

Compare to the active ingredient in FiberCon ®

BULK-FORMING / FIBER LAXATIVE

- GENTLE RELIEF OF CONSTIPATION
- WON’T CAUSE GAS OR BLOATING
- EFFECTIVE AS FIBER POWDERS

Distributed by: Xinhua Health Technology(HongKong)Co., Limited

Room 29 block a 13/f metropolitan fty & wh bldg 30-32chaiwan kok st tsuen wannt

90 Caplets